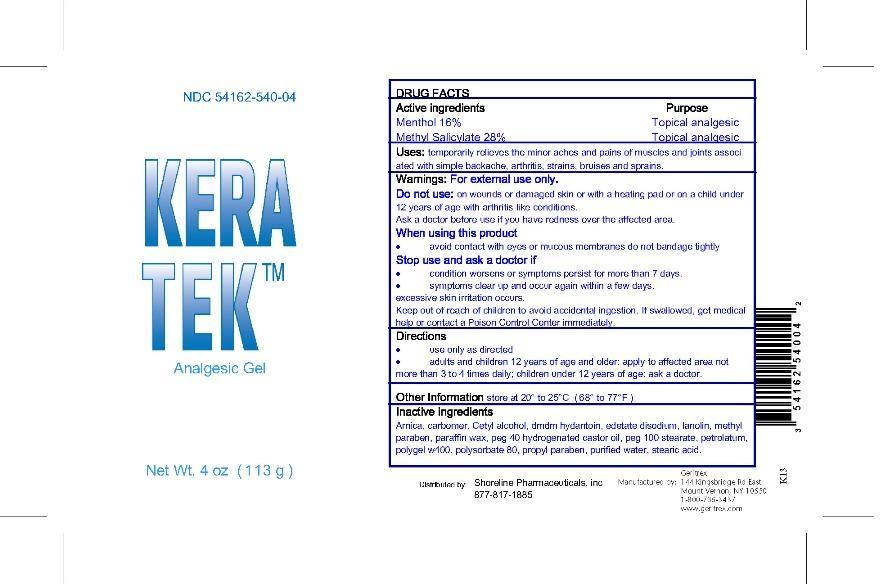 DRUG LABEL: KERATEK
NDC: 54162-540 | Form: GEL
Manufacturer: GERITREX CORP
Category: otc | Type: HUMAN OTC DRUG LABEL
Date: 20131021

ACTIVE INGREDIENTS: MENTHOL 16 g/100 g; METHYL SALICYLATE 28 g/100 g
INACTIVE INGREDIENTS: ARNICA MONTANA; CETYL ALCOHOL; DMDM HYDANTOIN; EDETATE DISODIUM; LANOLIN; METHYLPARABEN; PARAFFIN; PEG-40 CASTOR OIL; PEG-100 STEARATE; PETROLATUM; POLYSORBATE 80; PROPYLPARABEN; WATER; STEARIC ACID

KERATEK GEL

DRUG FACTS

Active Ingredients Purpose

Menthol 16% Topical analgesic

Methyl Salicylate 28% Topical analgesic

USES

Temporarily retieves the minor aches and pains of muscles and joints associated with single

backache, arthritis, strains, bruises and sprains.

Directions

Use only as directed

Adults and children 12 years of age and older apply to affected area not more than 3 to 4 times daily

children under 12 years of age ask a doctor

Warnings

For external use only

Do not use on wounds of damaged skin or with a heating pad or on a child under 12 years of age with arthritis-like conditions.

Ask doctor before use if you have redness over the affected area.

When using this product

Avoid contact with eyes or mucous membranes do not bandage tightly

Stop use and ask a doctor if

condition worsens or symptoms persist for more than 7 days

symtoms clear up and occur again within a few days

excessive skin irritation occurs

Inactive Ingredients

Arnica, carbomer, cetyl alcohol, dmdm hydantoin, edetate disodium, lanolin, methyl paraben, paraffin wax, peg 40 hydrogenated castor oil,

peg 100 stearate, petrolatum, polygel w400, polysorbate 80, propyl paraben, purified water, stearic acid.

Keep out of reach of children to avoid accidental ingestion. if swallowed, get medical help or

contact a Poison Control Center Immediately

STORAGE AND HANDLING

Store at 20' to 25'C (68' to 77'F)

DOSAGE AND ADMINISTRATION

Apply to affected area not more than 3 to 4 times daily.